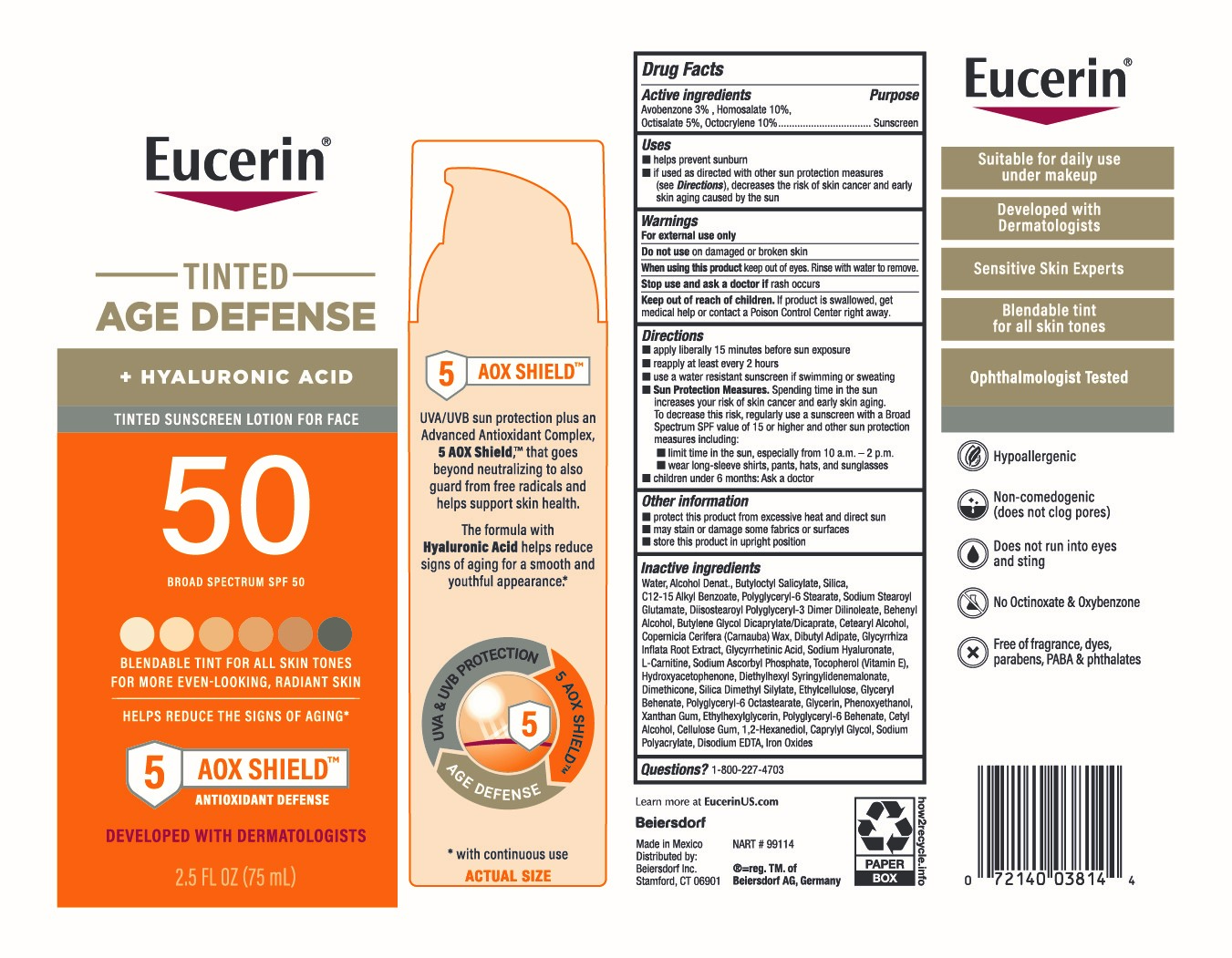 DRUG LABEL: Eucerin Tinted Age Defense Suncreen SPF 50
NDC: 66800-0381 | Form: LOTION
Manufacturer: Beiersdorf Inc
Category: otc | Type: HUMAN OTC DRUG LABEL
Date: 20251231

ACTIVE INGREDIENTS: OCTISALATE 5 g/100 g; AVOBENZONE 3 g/100 g; HOMOSALATE 10 g/100 g; OCTOCRYLENE 10 g/100 g
INACTIVE INGREDIENTS: DL-CARNITINE; ETHYLHEXYLGLYCERIN; 1,2-HEXANEDIOL; SILICA DIMETHYL SILYLATE; SODIUM STEAROYL GLUTAMATE; ALLANTOIN GLYCYRRHETINIC ACID; HYDROXYACETOPHENONE; SODIUM POLYACRYLATE (8000 MW); CAPRYLYL GLYCOL; BROWN IRON OXIDE; GLYCERIN; DOCOSANOL; CARNAUBA WAX; ETHYLCELLULOSE, UNSPECIFIED; POLYGLYCERYL-6 BEHENATE; DISODIUM EDTA-COPPER; WATER; ALKYL (C12-15) BENZOATE; DIBUTYL ADIPATE; SODIUM ASCORBYL PHOSPHATE; BUTYLOCTYL SALICYLATE; POLYGLYCERYL-6 STEARATE; DIISOSTEAROYL POLYGLYCERYL-3 DIMER DILINOLEATE; BUTYLENE GLYCOL DICAPRYLATE/DICAPRATE; CETOSTEARYL ALCOHOL; GLYCYRRHIZA INFLATA ROOT; XANTHAN GUM; CETYL ALCOHOL; CARBOXYMETHYLCELLULOSE SODIUM, UNSPECIFIED; SILICON DIOXIDE; HYALURONATE SODIUM; PHENOXYETHANOL; ALCOHOL; DIETHYLHEXYL SYRINGYLIDENEMALONATE; DIMETHICONE; TOCOPHEROL; ETHYLHEXYLGLYCERYL BEHENATE

Eucerin Tinted Age Defense SPF 50

Active ingredients

Avobenzone 3%, Homosalate 10%, Octisalate 5%, Octocrylene 10%

Purpose

Sunscreen

Uses

■ helps prevent sunburn

■ if used as directed with other sun protection measures (see Directions), decreases the risk of skin cancer and early skin aging caused by the sun

Warnings

For external use only

Do not useon damaged or broken skin

WHEN USING

When using this productkeep out of eyes. Rinse with water to remove.

Stop use and ask a doctor ifrash occurs

Keep out of reach of children.If product is swallowed, get medical help or contact a Poison Control Center right away.

Directions

■ apply liberally 15 minutes before sun exposure

■ reapply at least every 2 hours

■ use a water resistant sunscreen if swimming or sweating

■ Sun Protection Measures.Spending time in the sun increases your risk of skin cancer and early skin aging. To decrease this risk, regularly use a sunscreen with a Broad Spectrum SPF value of 15 or higher and other sun protection measures including:

■ limit time in the sun, especially from 10 a.m. – 2 p.m.

■ wear long-sleeve shirts, pants, hats, and sunglasses

■ children under 6 months: Ask a doctor

Other information

■ protect this product from excessive heat and direct sun

■ may stain or damage some fabrics or surfaces

■ store this product in upright position

Inactive ingredients

Water, Alcohol Denat., Butyloctyl Salicylate, Silica, C12-15 Alkyl Benzoate, Polyglyceryl-6 Stearate, Sodium Stearoyl Glutamate, Diisostearoyl Polyglyceryl-3 Dimer Dilinoleate, Behenyl Alcohol, Butylene Glycol Dicaprylate/Dicaprate, Cetearyl Alcohol, Copernicia Cerifera (Carnauba) Wax, Dibutyl Adipate, Glycyrrhiza Inflata Root Extract, Glycyrrhetinic Acid, Sodium Hyaluronate, L-Carnitine, Sodium Ascorbyl Phosphate, Tocopherol (Vitamin E), Hydroxyacetophenone, Diethylhexyl Syringylidenemalonate, Dimethicone, Silica Dimethyl Silylate, Ethylcellulose, Glyceryl Behenate, Polyglyceryl-6 Octastearate, Glycerin, Phenoxyethanol, Xanthan Gum, Ethylhexylglycerin, Polyglyceryl-6 Behenate, Cetyl Alcohol, Cellulose Gum, 1,2-Hexanediol, Caprylyl Glycol, Sodium Polyacrylate, Disodium EDTA, Iron Oxides

Questions?

1-800-227-4703

PACKAGE LABEL

Eucerin

Tinted Age Defense

+ Hyaluronic Acid Tinted Sunscreen Lotion For Face

50

Broad Spectrum SPF 50

Blendable Tint For All Skin Tone

For More Even-Looking, Radiant Skin

Helps Reduce the Signs of Aging*

5 AOX Shield AntioxidantDefense

Developed with Dermatologists